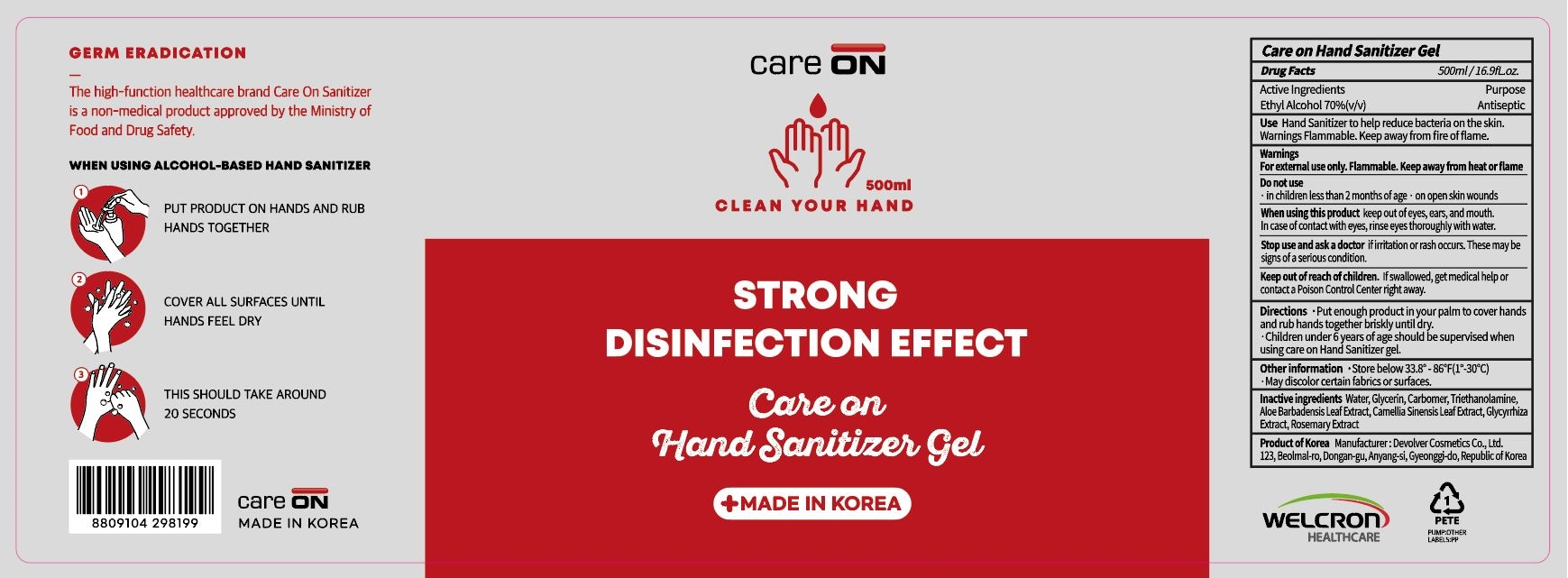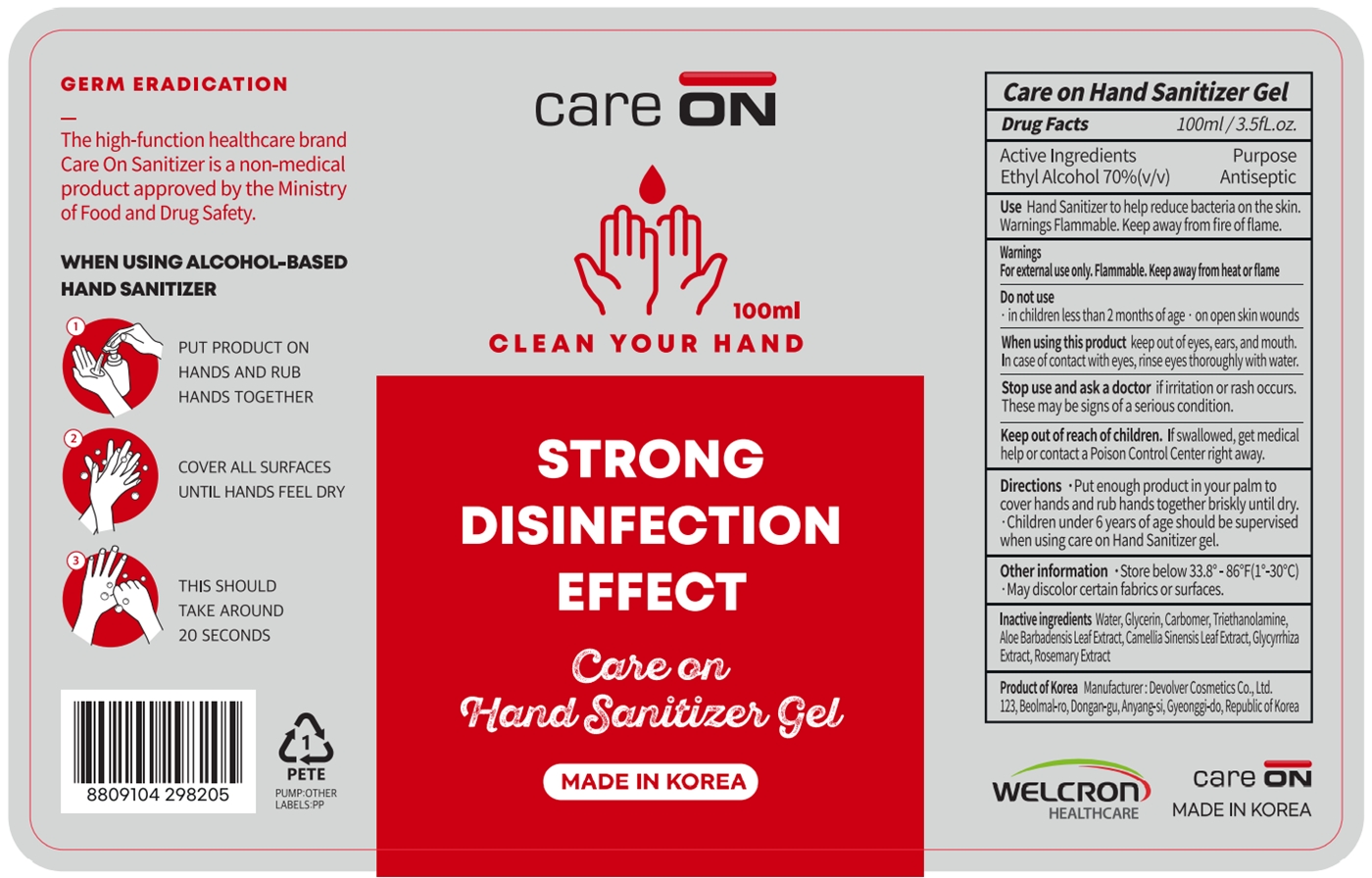 DRUG LABEL: CARE ON HAND SANITIZER Gel
NDC: 70416-2001 | Form: GEL
Manufacturer: WELCRON HEALTHCARE CO., LTD
Category: otc | Type: HUMAN OTC DRUG LABEL
Date: 20201119

ACTIVE INGREDIENTS: ALCOHOL 70 mL/100 mL
INACTIVE INGREDIENTS: WATER; CARBOMER HOMOPOLYMER, UNSPECIFIED TYPE; TROLAMINE; ALOE VERA LEAF; GREEN TEA LEAF; LICORICE; ROSEMARY; GLYCERIN

70416-2001

Active Ingredients

Ethyl Alcohol 70%

Purpose

Antiseptic

Use

Hand sanitizer to help reduce bacteria on the skin.

Warnings

For external use only. Flammable. Keep away from heat or flame.

Do not use

- in children less than 2 months of age
- on open skin wounds

When using this product

keep out of eyes, ears, and mouth.

In case of contact with eyes, rinse eyes thoroughly with water.

Stop use and ask a doctor

if irritation or rash occurs. These may be signs of a serious condition.

Keep out of reach of children.

If swallowed, get medical help or contact a Poison Control Center right away.

Directions

- Put enough product in your palm to cover hands and rub hands together briskly until dry.
- Children under 6 years of age should be supervised when using care on Hand Sanitizer gel.

Other information

- Store below 33.8-86F(1-30C)
- May discolor certain fabrics or surfaces.

Inactive ingredients

Water, Glycerin, Carbomer, Triethanolamine, Aloe Barbadensis Leaf Extract, Camellia Sinensis Leaf Extract, Glycyrrhiza Extract, Rosemary Extract